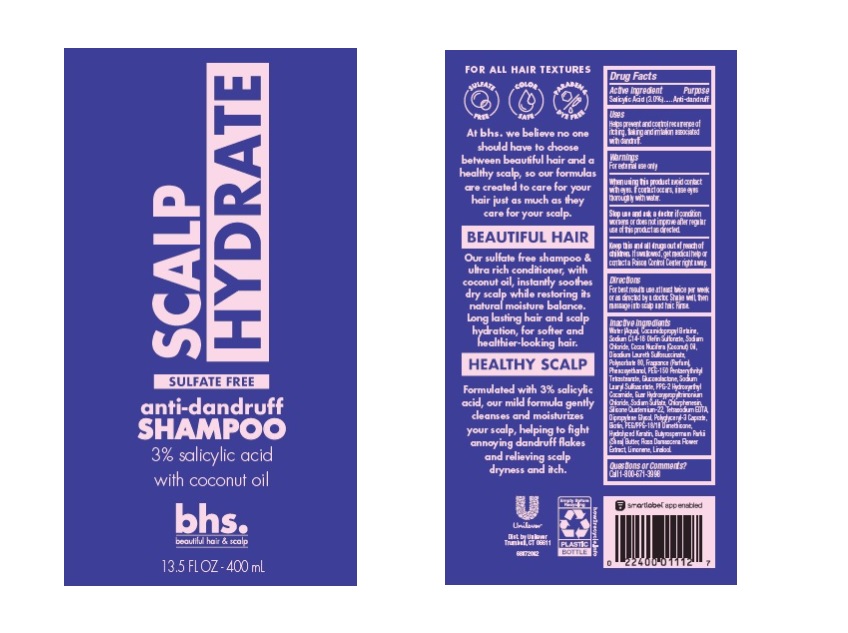 DRUG LABEL: bhs beautiful hair and scalp
NDC: 64942-2063 | Form: LIQUID
Manufacturer: Conopco, Inc. d/b/a/ Unilever
Category: otc | Type: HUMAN OTC DRUG LABEL
Date: 20241107

ACTIVE INGREDIENTS: SALICYLIC ACID 3 g/100 mL
INACTIVE INGREDIENTS: BIOTIN; COCONUT OIL; PHENOXYETHANOL; LIMONENE, (+)-; SODIUM C14-16 OLEFIN SULFONATE; POLYGLYCERYL-3 CAPRATE; DIPROPYLENE GLYCOL; WATER; COCAMIDOPROPYL BETAINE; SODIUM CHLORIDE; DISODIUM LAURETH SULFOSUCCINATE; POLYSORBATE 80; PEG-150 PENTAERYTHRITYL TETRASTEARATE; GLUCONOLACTONE; SODIUM LAURYL SULFOACETATE; PPG-2 HYDROXYETHYL COCAMIDE; GUAR HYDROXYPROPYLTRIMONIUM CHLORIDE (1.7 SUBSTITUENTS PER SACCHARIDE); SODIUM SULFATE; CHLORPHENESIN; EDETATE SODIUM; LINALOOL, (+/-)-; ROSA DAMASCENA FLOWER; PEG/PPG-18/18 DIMETHICONE; SHEA BUTTER

bhs. beautiful hair & scalp Scalp Hydrate Anti-dandruff Shampoo

Drug Facts

Active ingredient

Salicylic Acid (3.0%)

Purpose

Anti-dandruff

Use

Helps prevent and control recurrence of itching, flaking and irritation associated with dandruff.

Warnings

For external use only

When using this product avoid contact with eyes. If contact occurs, rinse eyes thoroughtly with water.

Stop use and ask a doctor if condition worsens or does not improve after regular use of this product as directed.

KEEP OUT OF REACH OF CHILDREN

Keep this and all drugs out of reach of children.
If swallowed, get medical help or contact a Poison Control Center right away.

Directions

For best results use at least twice per week or as directed by a doctor. Shake well, then massage into scalp and hair. Rinse.

Inactive Ingredients

Water (Aqua), Cocamidopropyl Betaine, Sodium C14-16 Olefin Sulfonate, Sodium Chloride, Cocos Nucifera (Coconut) Oil, Disodium Laureth Sulfosuccinate, Polysorbate 80, Fragrance (Parfum), Phenoxyethanol, PEG-150 Pentaerythrityl Tetrastearate, Gluconolactone, Sodium Lauryl Sulfoacetate, PPG-2 Hydroxyethyl Cocamide, Guar Hydroxypropyltrimonium Chloride, Sodium Sulfate, Chlorphenesin, Silicone Quaternium-22, Tetrasodium EDTA, Dipropylene Glycol, Polyglyceryl-3 Caprate, Biotin, PEG/PPG-18/18 Dimethicone, Hydrolyzed Keratin, Butyrospermum Parkii (Shea) Butter, Rosa Damascena Flower Extract, Limonene, Linalool.

Questions or comments?

Call 1-800-671-3998